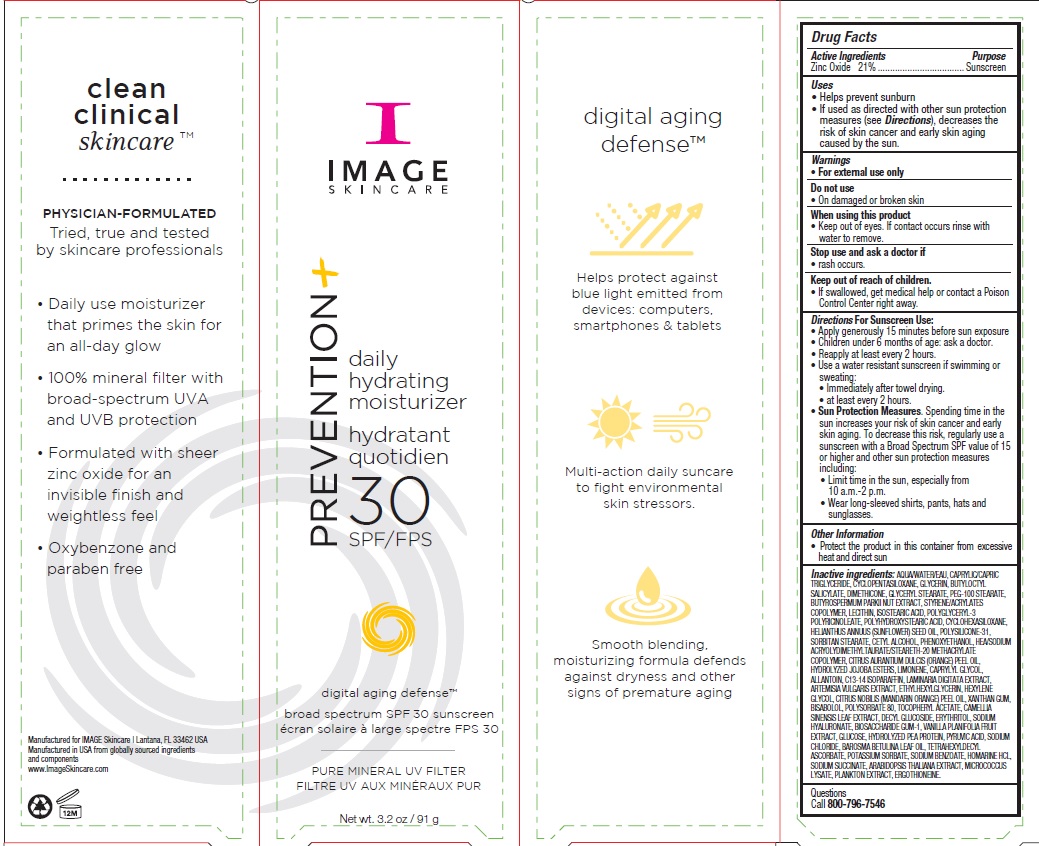 DRUG LABEL: Prevention Plus Daily Hydrating Moisturizer SPF 30
NDC: 62742-4183 | Form: CREAM
Manufacturer: Allure Labs Inc
Category: otc | Type: HUMAN OTC DRUG LABEL
Date: 20191211

ACTIVE INGREDIENTS: ZINC OXIDE 210 mg/1 g
INACTIVE INGREDIENTS: WATER; MEDIUM-CHAIN TRIGLYCERIDES; CYCLOMETHICONE 5; GLYCERIN; BUTYLOCTYL SALICYLATE; DIMETHICONE; GLYCERYL MONOSTEARATE; PEG-100 STEARATE; SHEANUT; STYRENE/ACRYLAMIDE COPOLYMER (500000 MW); LECITHIN, SOYBEAN; ISOSTEARIC ACID; POLYGLYCERYL-3 RICINOLEATE; POLYHYDROXYSTEARIC ACID (2300 MW); CYCLOMETHICONE 6; SUNFLOWER OIL; POLYSILICONE-15; SORBITAN MONOSTEARATE; CETYL ALCOHOL; PHENOXYETHANOL; HYDROXYETHYL ACRYLATE/SODIUM ACRYLOYLDIMETHYL TAURATE COPOLYMER (100000 MPA.S AT 1.5%); STEARETH-20 METHACRYLATE; CITRUS AURANTIUM FRUIT OIL; HYDROLYZED JOJOBA ESTERS (ACID FORM); LIMONENE, (+)-; CAPRYLYL GLYCOL; ALLANTOIN; C13-14 ISOPARAFFIN; LAMINARIA DIGITATA; ARTEMISIA VULGARIS WHOLE; ETHYLHEXYLGLYCERIN; HEXYLENE GLYCOL; MANDARIN OIL; XANTHAN GUM; LEVOMENOL; POLYSORBATE 80; .ALPHA.-TOCOPHEROL ACETATE; TRIETHOXYCAPRYLYLSILANE; GREEN TEA LEAF; DECYL GLUCOSIDE; ERYTHRITOL; HYALURONATE SODIUM; BIOSACCHARIDE GUM-1; VANILLA; ANHYDROUS DEXTROSE; PEA PROTEIN; PYRUVIC ACID; SODIUM CHLORIDE; AGATHOSMA BETULINA LEAF OIL; TETRAHEXYLDECYL ASCORBATE; POTASSIUM SORBATE; SODIUM BENZOATE; HOMARINE HYDROCHLORIDE; SODIUM SUCCINATE ANHYDROUS; ARABIDOPSIS THALIANA; MICROCOCCUS LUTEUS; ANACYSTIS NIDULANS; ERGOTHIONEINE

DRUG FACTS

Active Ingredients:

Zinc Oxide 21.0%

Purpose: Sunscreen

Uses:

- Helps prevent sunburn.
- If used as directed with other sun protection measures, decreases the risk of skin cancer and early skin aging caused by the sun.

WARNINGS AND PRECAUTIONS

Warning: For external use only.

Do not use: on damaged or broken skin.

When using this products:

- Keep out of eyes.If contact occurs rinse with water to remove.

Stop use and ask a doctor if :rash occurs.

Keep out of reach of children:

- If swallowed, get medical help or contact a Poison Control Center right away.

DOSAGE AND ADMINISTRATION

Directions For Sunscreen Use:

- Apply generously 15 minutes before sun exposure.
- Children under 6 months of age: ask a doctor.
- Reapply at least every 2 hours.
- Use a water resistant sunscreen if swimming or sweating.
- Immediatly after towel drying.
- at least every 2 hours.
- Sun protection measures.Spending time in the sun increase your risk of skin cancer and early skin aging. To decrease this risk, regularly use a sunscreen with a Broad Spectrum SPF value of 15 or higher and other sun protection measures including:
- limit time in the sun, especially from 10 a.m. - 2 p.m.
- wear long-sleeved shirts, pants, hats and sunglasses.

OTHER SAFETY INFORMATION

Protect the product in this container from excessive heat and direct sun.

INACTIVE INGREDIENT

Inactive ingredients: AQUA/WATER/EAU, CAPRYLIC/CAPRIC TRIGLYCERIDE, CYCLOPENTASILOXANE, GLYCERIN, BUTYLOCTYL SALICYLATE, DIMETHICONE, GLYCERYL STEARATE, PEG-100 STEARATE, BUTYROSPERMUM PARKII NUT EXTRACT, STYRENE/ACRYLATES COPOLYMER, LECITHIN, ISOSTEARIC ACID, POLYGLYCERYL-3 POLYRICINOLEATE, POLYHYDROXYSTEARIC ACID, CYCLOHEXASILOXANE, HELIANTHUS ANNUUS (SUNFLOWER) SEED OIL, POLYSILICONE-31, SORBITAN STEARATE, CETYL ALCOHOL, PHENOXYETHANOL, HEA/SODIUM ACRYOLYDIMETHYLTAURATE/STEARETH-20 METHACRYLATE COPOLYMER, CITRUS AURANTIUM DULCIS (ORANGE) PEEL OIL, HYDROLYZED JOJOBA ESTERS, LIMONENE, CAPRYLYL GLYCOL, ALLANTOIN, C13-14 ISOPARAFFIN, LAMINARIA DIGITATA EXTRACT, ARTEMISIA VULGARIS EXTRACT, ETHYLHEXYLGLYCERIN, HEXYLENE GLYCOL, CITRUS NOBILIS (MANDARIN ORANGE) PEEL OIL, XANTHAN GUM, BISABOLOL, POLYSORBATE 80, TOCOPHERYL ACETATE, CAMELLIA SINENSIS LEAF EXTRACT, DECYL GLUCOSIDE, ERYTHRITOL, SODIUM HYALURONATE, BIOSACCHARIDE GUM-1, VANILLA PLANIFOLIA FRUIT EXTRACT, GLUCOSE, HYDROLYZED PEA PROTEIN, PYRUVIC ACID, SODIUM CHLORIDE, BAROSMA BETULINA LEAF OIL, TETRAHEXYLDECYL ASCORBATE, POTASSIUM SORBATE, SODIUM BENZOATE, HOMARINE HCL, SODIUM SUCCINATE, ARABIDOPSIS THALIANA EXTRACT, MICROCOCCUS LYSATE, PLANKTON EXTRACT, ERGOTHIONEINE.

PACKAGE LABEL

Manufactured for IMAGE Skincare, Lantana, FL 33462 USA

Manufactured in USA from globally sourced ingredients and components

www.ImageSkincare.com

QUESTIONS

Call 800-796-7546